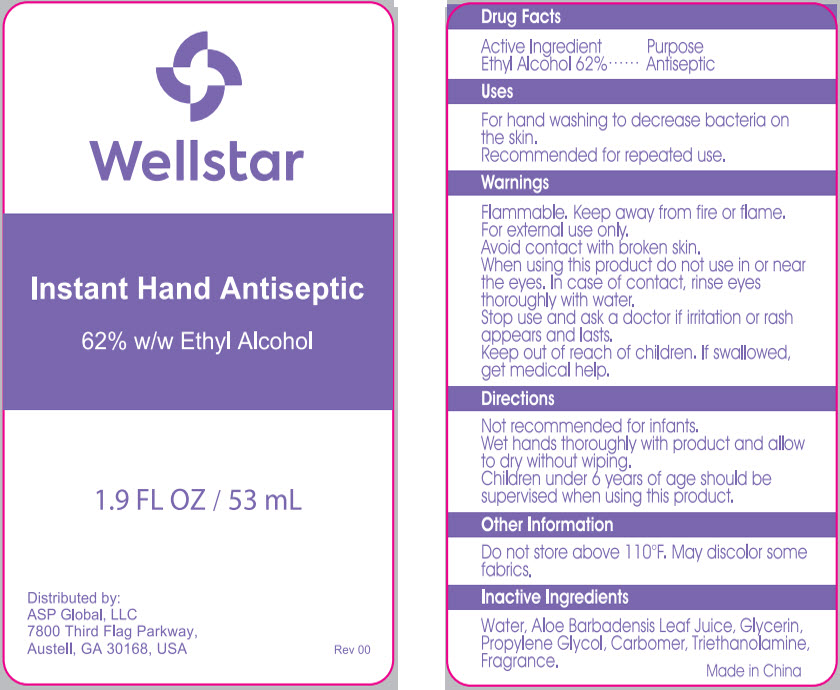 DRUG LABEL: Instant Hand Antiseptic
NDC: 59448-008 | Form: GEL
Manufacturer: ASP Global
Category: otc | Type: HUMAN OTC DRUG LABEL
Date: 20241206

ACTIVE INGREDIENTS: ALCOHOL 62 mL/100 mL
INACTIVE INGREDIENTS: WATER; ALOE VERA LEAF; GLYCERIN; PROPYLENE GLYCOL; CARBOMER INTERPOLYMER TYPE A (ALLYL SUCROSE CROSSLINKED); TROLAMINE

Instant Hand Antiseptic

Drug Facts

Active Ingredient

Ethyl Alcohol 62%

Purpose

Antiseptic

Uses

For hand washing to decrease bacteria on the skin.

Recommended for repeated use.

Warnings

Flammable. Keep away from fire or flame.

For external use only.

Avoid contact with broken skin.

When using this product do not use in or near the eyes. In case of contact, rinse eyes thoroughly with water.

Stop use and ask a doctor if irritation or rash appears and lasts.

Keep out of reach of children. If swallowed, get medical help.

Directions

Not recommended for infants.

Wet hands thoroughly with product and allow to dry without wiping.

Children under 6 years of age should be supervised when using this product.

Other Information

Do not store above 110°F. May discolor some fabrics.

Inactive Ingredients

Water, Aloe Barbadensis Leaf Juice, Glycerin, Propylene Glycol, Carbomer, Triethanolamine, Fragrance.

Distributed by:
ASP Global, LLC
7800 Third Flag Parkway,
Austell, GA 30168, USA

PRINCIPAL DISPLAY PANEL - 53 mL Bottle Label

Wellstar

Instant Hand Antiseptic

62% w/w Ethyl Alcohol

1.9 FL OZ / 53 mL

Distributed by:
ASP Global, LLC
7800 Third Flag Parkway,
Austell, GA 30168, USA

Rev 00